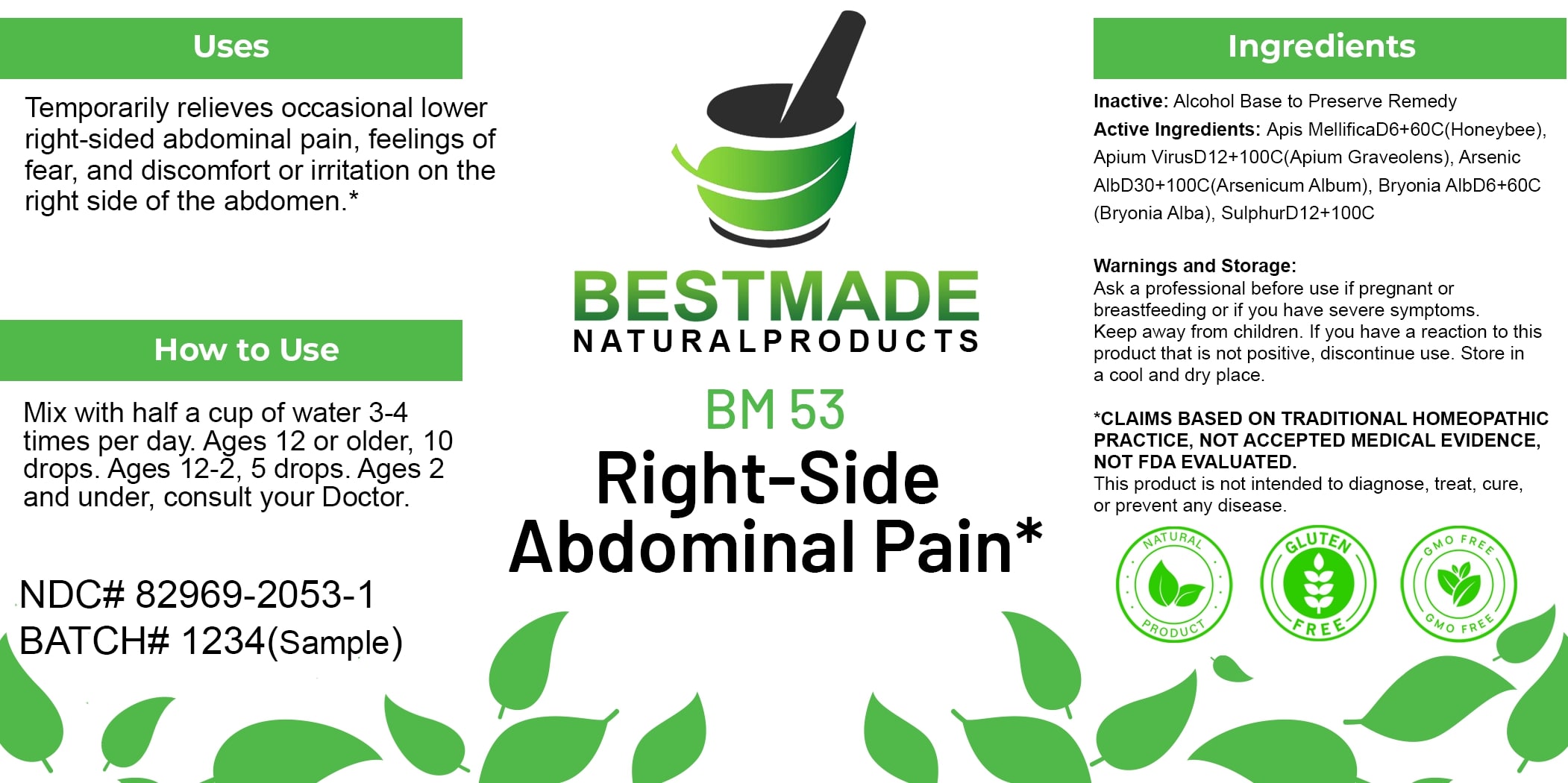 DRUG LABEL: Bestmade Natural Products BM53
NDC: 82969-2053 | Form: LIQUID
Manufacturer: Bestmade Natural Products
Category: homeopathic | Type: HUMAN OTC DRUG LABEL
Date: 20250123

ACTIVE INGREDIENTS: APIS MELLIFERA 60 [hp_C]/100 [hp_C]; CELERY SEED 100 [hp_C]/100 [hp_C]; BRYONIA ALBA ROOT 60 [hp_C]/100 [hp_C]; SULFUR 100 [hp_C]/100 [hp_C]; ARSENIC TRIOXIDE 100 [hp_C]/100 [hp_C]
INACTIVE INGREDIENTS: ALCOHOL 100 [hp_C]/100 [hp_C]

BM53

DOSAGE AND ADMINISTRATION

How to Use

Mix with half a cup of water 3-4 times per day. Ages 12 or older, 10 drops. Ages 12-2, 5 drops. Ages 2 and under, consult your Doctor.

INACTIVE INGREDIENT

Ingredients

Inactive: Alcohol Base to Preserve Remedy

ACTIVE INGREDIENT

Active Ingredients: Apis Mellifica D6+60C (Honeybee), Apium Virus D12+100C (Apium Graveolens), Arsenic Alb D30+100C (Arsenicum Album), Bryonia Alb D6+60C (Bryonia Alba), Sulphur D12+100C

Uses

Temporarily relieves occasional lower right-sided abdominal pain, feelings of fear, and discomfort or irritation on the right side of the abdomen.*

*CLAIMS BASED ON TRADITIONAL HOMEOPATHIC PRACTICE, NOT ACCEPTED MEDICAL EVIDENCE. NOT FDA EVALUATED.

This product is not intended to diagnose, treat, cure, or prevent any disease.

Uses

Temporarily relieves occasional lower right-sided abdominal pain, feelings of fear, and discomfort or irritation on the right side of the abdomen.*

*CLAIMS BASED ON TRADITIONAL HOMEOPATHIC PRACTICE, NOT ACCEPTED MEDICAL EVIDENCE. NOT FDA EVALUATED.

This product is not intended to diagnose, treat, cure, or prevent any disease.

KEEP OUT OF REACH OF CHILDREN

Warnings and Storage:

Ask a professional before use if pregnant or breastfeeding or if you have severe symptoms. Keep away from children. If you have a reaction to this product that is not positive, discontinue use. Store in a cool and dry place.

Warnings and Storage:

Ask a professional before use if pregnant or breastfeeding or if you have severe symptoms. Keep away from children. If you have a reaction to this product that is not positive, discontinue use. Store in a cool and dry place.

*CLAIMS BASED ON TRADITIONAL HOMEOPATHIC PRACTICE, NOT ACCEPTED MEDICAL EVIDENCE. NOT FDA EVALUATED.

This product is not intended to diagnose, treat, cure, or prevent any disease.

Entire package label